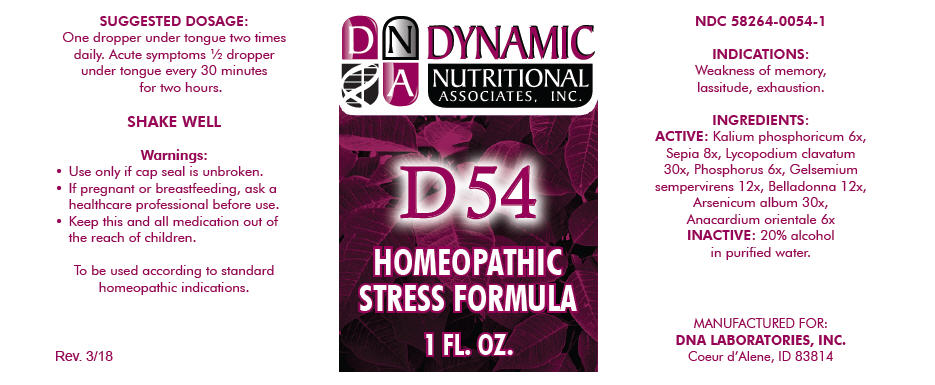 DRUG LABEL: D-54
NDC: 58264-0054 | Form: SOLUTION
Manufacturer: DNA Labs, Inc.
Category: homeopathic | Type: HUMAN OTC DRUG LABEL
Date: 20250113

ACTIVE INGREDIENTS: DIBASIC POTASSIUM PHOSPHATE 6 [hp_X]/1 mL; SEPIA OFFICINALIS JUICE 8 [hp_X]/1 mL; LYCOPODIUM CLAVATUM SPORE 30 [hp_X]/1 mL; PHOSPHORUS 6 [hp_X]/1 mL; GELSEMIUM SEMPERVIRENS ROOT 12 [hp_X]/1 mL; ATROPA BELLADONNA 12 [hp_X]/1 mL; ARSENIC TRIOXIDE 30 [hp_X]/1 mL; SEMECARPUS ANACARDIUM JUICE 6 [hp_X]/1 mL
INACTIVE INGREDIENTS: ALCOHOL; WATER

D-54

NDC 58264-0054-1

INDICATIONS

PURPOSE

Weakness of memory, lassitude, exhaustion.

INGREDIENTS

ACTIVE

Kalium phosphoricum 6x, Sepia 8x, Lycopodium clavatum 30x, Phosphorus 6x, Gelsemium sempervirens 12x, Belladonna 12x, Arsenicum album 30x, Anacardium orientale 6x

INACTIVE

20% alcohol in purified water.

SUGGESTED DOSAGE

One dropper under tongue two times daily. Acute symptoms ½ dropper under tongue every 30 minutes for two hours.

STORAGE AND HANDLING

SHAKE WELL

Warnings

- Use only if cap seal is unbroken.

PREGNANCY OR BREAST FEEDING

- If pregnant or breastfeeding, ask a healthcare professional before use.

KEEP OUT OF REACH OF CHILDREN

- Keep this and all medication out of the reach of children.

To be used according to standard homeopathic indications.

PRINCIPAL DISPLAY PANEL - 1 FL. OZ. Bottle Label

DYNAMIC
NUTRITIONAL
ASSOCIATES, INC.

D 54

HOMEOPATHIC
STRESS FORMULA

1 FL. OZ.